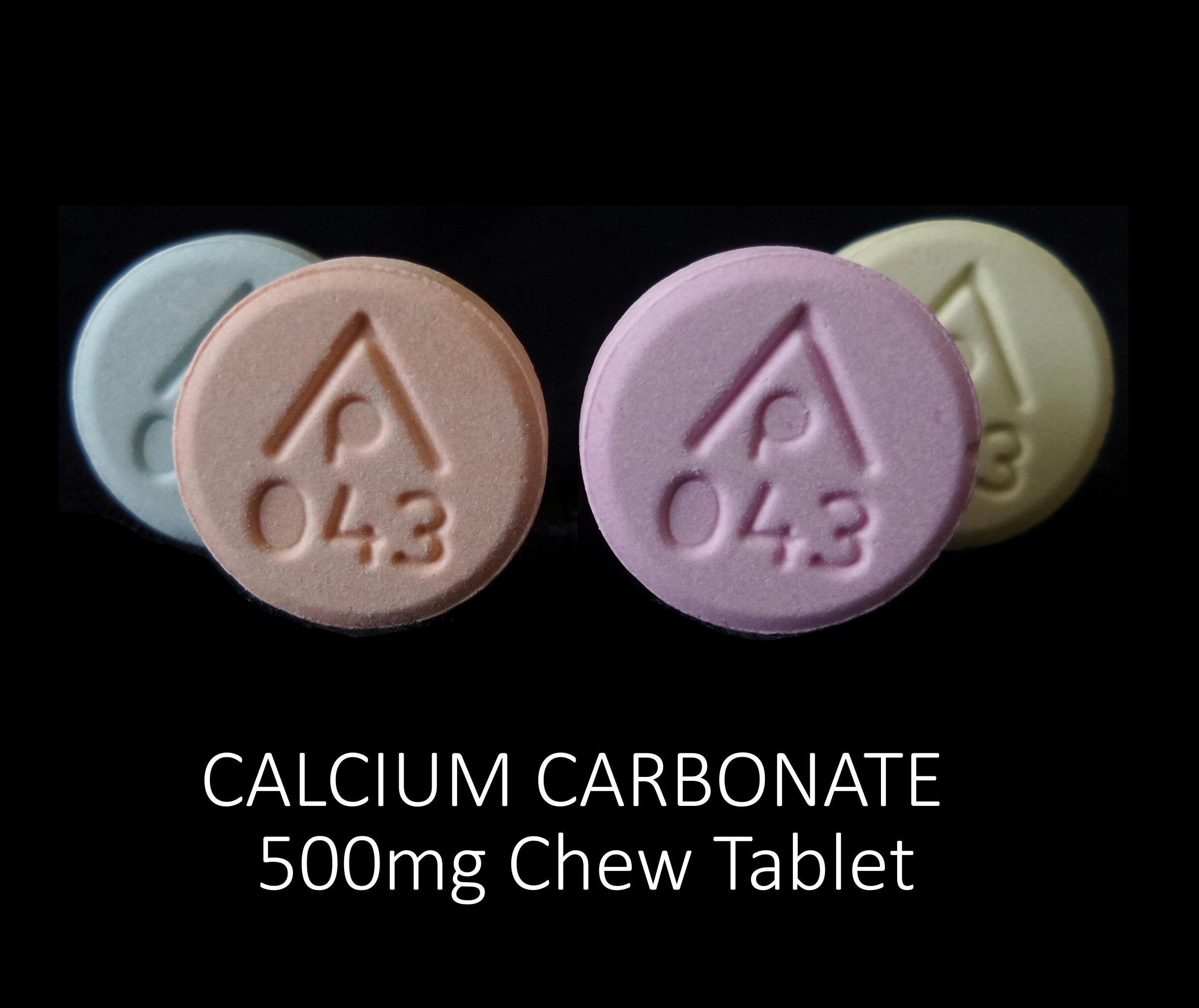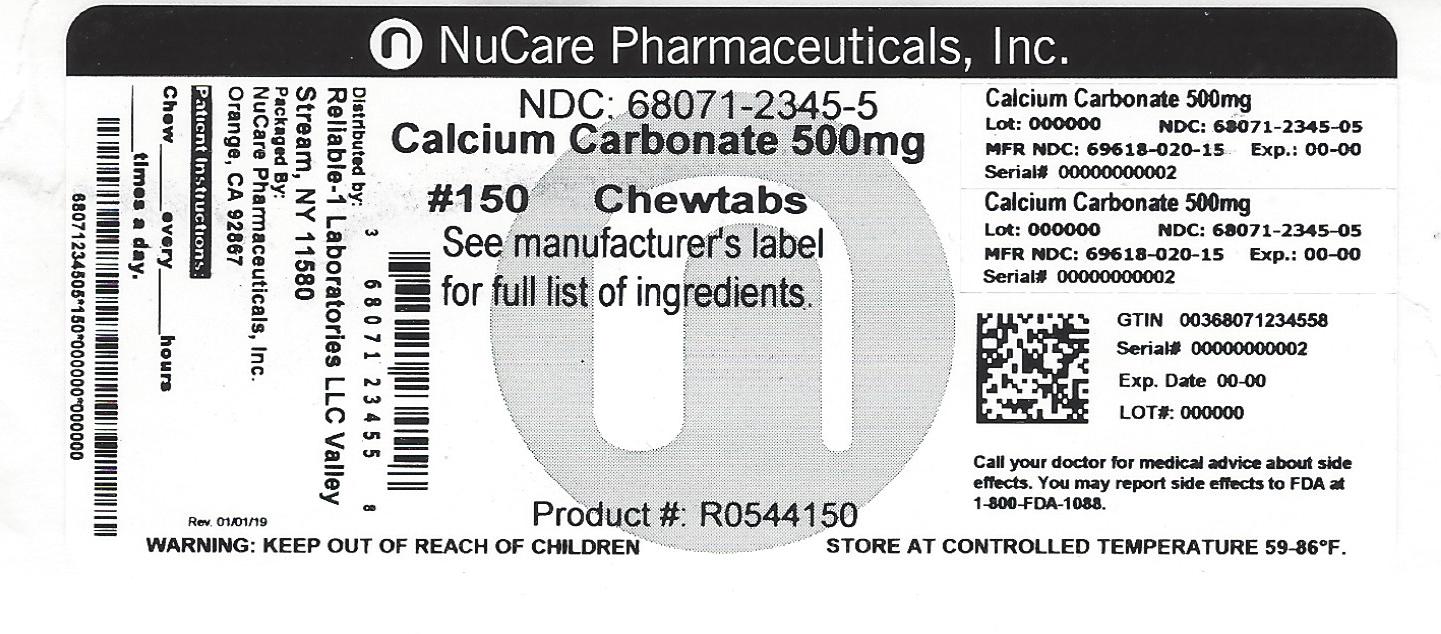 DRUG LABEL: Calcium Carbonate 500 mg
NDC: 68071-2345 | Form: TABLET, CHEWABLE
Manufacturer: NuCare Pharmaceuticals,Inc.
Category: otc | Type: HUMAN OTC DRUG LABEL
Date: 20260219

ACTIVE INGREDIENTS: CALCIUM CARBONATE 500 mg/1 1
INACTIVE INGREDIENTS: FD&C BLUE NO. 1; FD&C YELLOW NO. 6; MAGNESIUM STEARATE; D&C YELLOW NO. 10; D&C RED NO. 27; DEXTROSE

Calcium Carbonate 500 mg

Drug Facts

Active ingredient (in each chewable tablet)

Calcium carbonate 500 mg

Purpose

Antacid

INDICATIONS AND USAGE

Uses relieves

- acid indigestion
- heartburn
- sour stomach

Warnings

Ask a doctor or pharmacist before use if you are taking a prescription drug. Antacids may interact with certain prescription drugs.

Stop use and ask a doctor if symptoms last more than 2 weeks

Keep out of reach of children.

Ask a doctor or pharmacist before use if you are taking a prescription drug. Antacids may interact with certain prescription drugs.

Stop use and ask doctor if symptoms last more than 2 weeks

Keep out of reach of children.

Directions

Adults and children 12 years and over:

- chew 2-4 tablets as symptoms occur
- do not take more than 8 tablets in 24 hours
- do not use the maximum dosage for more than 2 weeks

children under 12 years:

ask a doctor

Other information

- each tablet contains: calcium 200 mg
- store at room temperature

Inactive ingredients

Al-lakes (D&C red #27, D&C yellow #10, FD&C blue #1, FD&C yellow #6), dextrose, flavors, magnesium stearate, maltodextrin

Questions or comments?

call 516-341-0666, 8:30 am - 4:30 pm ET, Monday-Friday